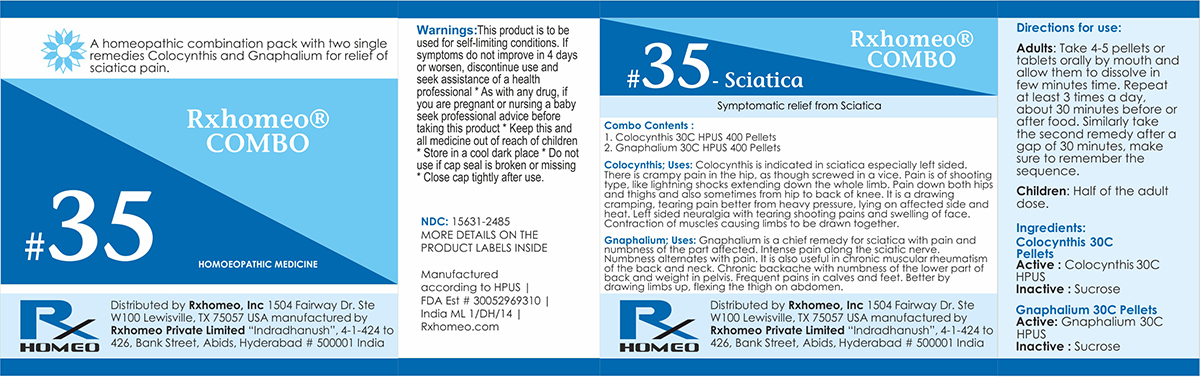 DRUG LABEL: Rxhomeo Homeopathic Combo-35
NDC: 15631-2485 | Form: KIT | Route: ORAL
Manufacturer: Rxhomeo Private Limited d.b.a.
Category: homeopathic | Type: HUMAN OTC DRUG LABEL
Date: 20161014

ACTIVE INGREDIENTS: CITRULLUS COLOCYNTHIS FRUIT PULP 3 [hp_X]/1 1; PSEUDOGNAPHALIUM OBTUSIFOLIUM 1 [hp_X]/1 1
INACTIVE INGREDIENTS: SUCROSE; LACTOSE

ACTIVE INGREDIENT

COLOCYNTHIS HPUS 3X and Higher

GNAPHALIUM POLYCEPHALUM HPUS 1X and Higher

USES

A homeopathic combination pack with two single remedies Colocynthis and Gnaphalium for relief of sciatica pain.

Colocynthis;Uses: Colocynthis is indicated in sciatica especially left sided. There is crampy pain in the hip, as though screwed in a vice. Pain is of shooting type, like lightning shocks extending down the whole limb. Pain down both hips and thighs and also sometimes from hip to back of knee. It is a drawing cramping, tearing pain better from heavy pressure, lying on affected side and heat. Left sided neuralgia with tearing shooting pains and swelling of face. Contraction of muscles causing limbs to be drawn together.

Gnaphalium;Uses: Gnaphalium is a chief remedy for sciatica with pain and numbness of the part affected. Intense pain along the sciatic nerve. Numbness alternates with pain. It is also useful in chronic muscular rheumatism of the back and neck. Chronic backache with numbness of the lower part of back and weight in pelvis. Frequent pains in calves and feet. Better by drawing limbs up, flexing the thigh on abdomen.

INDICATIONS

Condition listed above or as directed by the physician

DOSAGE

PELLETS included in the Combo

Adults- Take 4 or 6 Pellets by mouth, three times daily or as suggested by physician. Children 2 years and older- take 1/2 the adult dose.

WARNINGS

This product is to be used for self-limiting conditions

STOP USE

If symptoms do not improve in 4 days, or worsen, discontinue use and seek assistance of health professional

KEEP OUT OF REACH OF CHILDREN

Keep this and all medication out of reach of children

Do not use if capseal is broken or missing.

Close the cap tightly after use.

INACTIVE INGREDIENTS

Sucrose for Pellets.

STORAGE

Store in a cool dark place

QUESTIONS OR COMMENTS

www.Rxhomeo.com | 1.888.2796642 | info@rxhomeo.com
Rxhomeo, Inc 1504 Fairway Dr. Ste W 100 Lewisville, TX 75057 USA